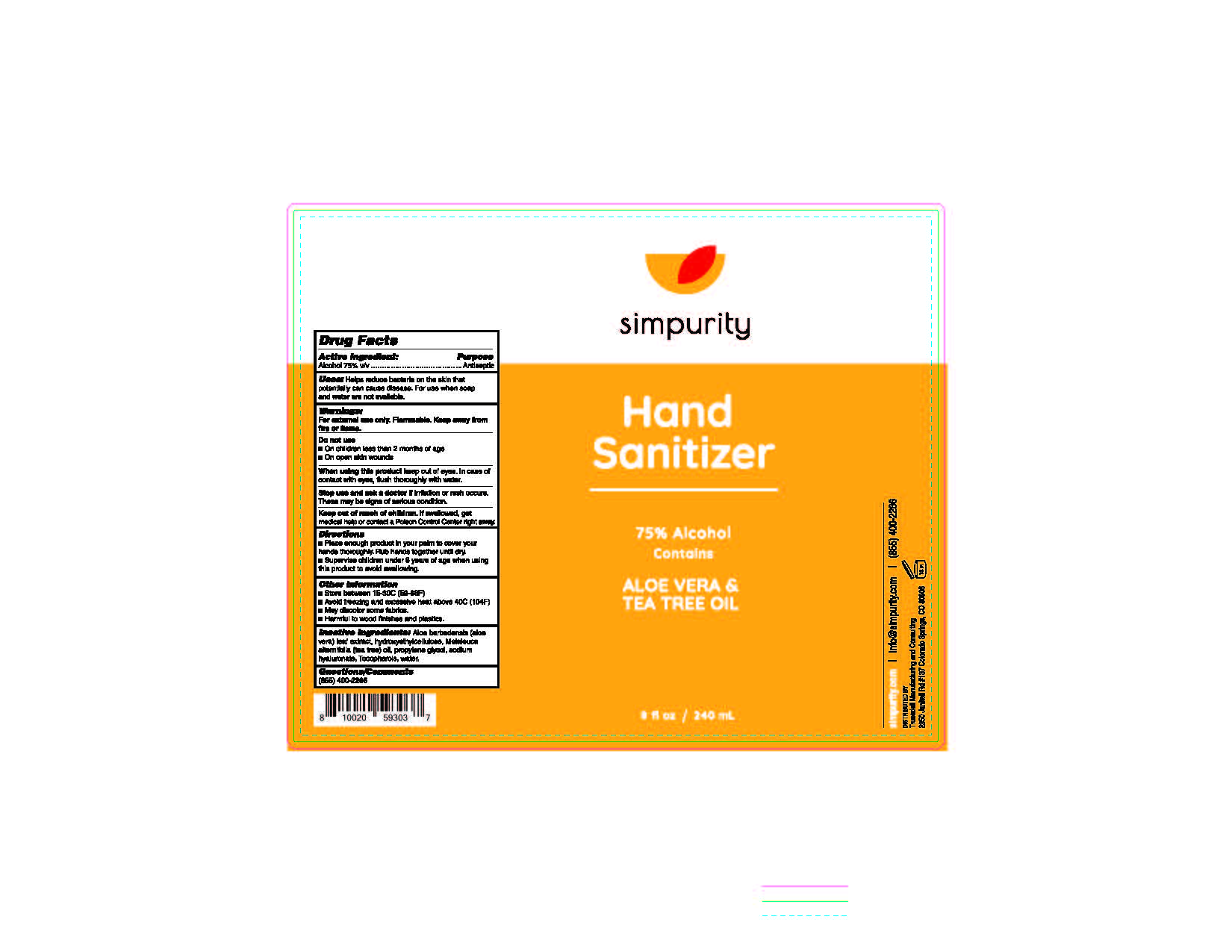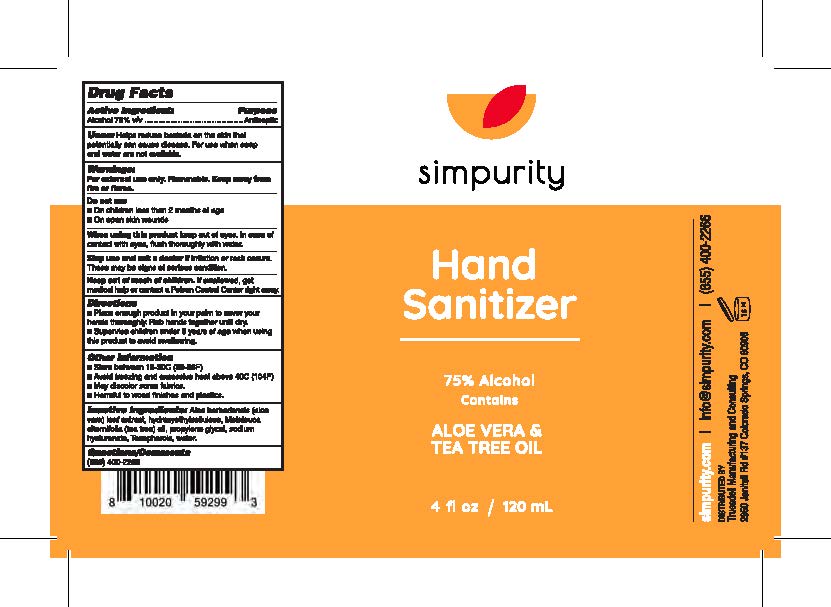 DRUG LABEL: Simpurity Hand Sanitizer
NDC: 74069-002 | Form: GEL
Manufacturer: Truesdell Manufacturing & Consulting, LLC
Category: otc | Type: HUMAN OTC DRUG LABEL
Date: 20211220

ACTIVE INGREDIENTS: ALCOHOL 75 mL/100 mL
INACTIVE INGREDIENTS: TOCOPHEROL 0.25 mL/100 mL; ALOE VERA LEAF 0.25 mL/100 mL; PROPYLENE GLYCOL 2 mL/100 mL; HYDROXYETHYL CELLULOSE, UNSPECIFIED 0.59 mL/100 mL; WATER 21.65 mL/100 mL; HYALURONATE SODIUM 0.01 mL/100 mL; TEA TREE OIL 0.25 mL/100 mL

Simpurity Hand Sanitizer, 4 oz.

Simpurity 75% alcohol Hand Sanitizer

This is a hand sanitizer manufactured according to the 1994 tentative final monograph for consumer antiseptics.

The hand sanitizer is manufactured using only the following United States Pharmacopoeia (USP) grade ingredients in the preparation of the product (percentage in final product formulation):

1. Alcohol (ethanol) (USP or Food Chemical Codex (FCC) grade) (75%, volume/volume (v/v)) in an aqueous solution denatured according to Alcohol and Tobacco Tax and Trade Bureau regulations in 27 CFR part 20.
2. hydroxyethylcellulose
3. aloe powder
4. propylene glycol
5. hyaluronic acid
6. tea tree essential oil
7. vitamin E
8. Sterile distilled water or boiled cold water.

The firm does not add other active or inactive ingredients. The product has undergone finished formulation product testing (kill study) to confirm effifacy and safety.

Active Ingredient(s)

Alcohol 75% v/v. Purpose: Antiseptic

Purpose

Antiseptic, Hand Sanitizer

Uses

Helps reduce bacteria on the skin that potentially can cause disease. For use when soap and water are not available.

Warnings

For external use only. Flammable. Keep away from heat or flame

Do not use

- in children less than 2 months of age
- on open skin wounds

When using this product keep out of eyes, ears, and mouth. In case of contact with eyes, rinse eyes thoroughly with water.
Stop use and ask a doctor if irritation or rash occurs. These may be signs of a serious condition.
Keep out of reach of children. If swallowed, get medical help or contact a Poison Control Center right away.

Stop use and ask a doctor if irritation or rash occurs. These may be signs of a serious condition.

Keep out of reach of children. If swallowed, get medical help or contact a Poison Control Center right away.

Directions

Place enough product on hands to cover all surfaces. Rub hands together until dry.
Supervise children under 6 years of age when using this product to avoid swallowing.

Other information

- Store between 15-30C (59-86F)
- Avoid freezing and excessive heat above 40C (104F)

Inactive ingredients

distilled water
hydroxyethylcellulose
aloe powder
propylene glycol
hyaluronic acid
tea tree essential oil
vitamin E

74069-002-08 240 mL Package Label - Principal Display Panel

240 mL NDC: 074069-002-08

74069-002-04 Principal Display Panel

120 mL NDC: 074069-002-04